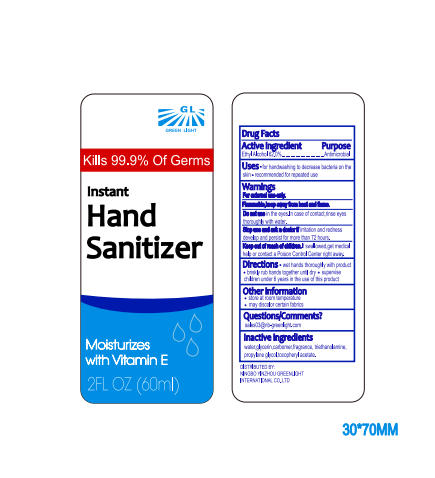 DRUG LABEL: Instant Hand Sanitizer
NDC: 77125-001 | Form: GEL
Manufacturer: Ningbo Yinzhou Lvguang International Trade Co.,Ltd
Category: otc | Type: HUMAN OTC DRUG LABEL
Date: 20200505

ACTIVE INGREDIENTS: ALCOHOL 37.2 mL/60 mL
INACTIVE INGREDIENTS: TRIETHANOLAMINE DODECYLBENZENESULFONATE 0.6 mL/60 mL; TOCOPHEROL 0.3 mL/60 mL; CARBOMER HOMOPOLYMER, UNSPECIFIED TYPE 0.18 mL/60 mL; GLYCERIN 0.6 mL/60 mL; PROPYLENE GLYCOL 0.6 mL/60 mL; WATER 20.52 mL/60 mL

Instant Hand Sanitizer

Active Ingredient

Ethyl Alcohol 62.0% Antimicrobial

Purpose

Purpose - Antimicrobial

Uses

- for handwashing to decrease bacteria on the skin
- recommended for repeated use

Warnings

For external use only

Flammable, keep away from heat and flame.

Do not use in the eyes, in case of contact, rinse eyes throughly with water.

Stop use and ask a doctor if irritation and redness develop and persist for more then 72 hours

Keep out of reach children

Keep out of reach of children, If swallowed, get medical help or contact a Poison Control Center right away.

Directions

- wet hands thoughly with product
- briskly rub hands together until dry
- supervise children 6 years of age in the use of this product

Other Information

- store at room temperature
- may discolor certain fabrics

Questions/Comments

sales03@nb-greenlight.com

DISTRIBUTED BY:
NINGBO YINZHOU GREENLIGHT INTERNATIONAL CO.,LTD

Inactive Ingredients

water,glycerin,carbomer, fragrance, triethanolamine, propylene glycol, tocopheryl acetate

Package Label

77125-001-01 NDC 60 ml